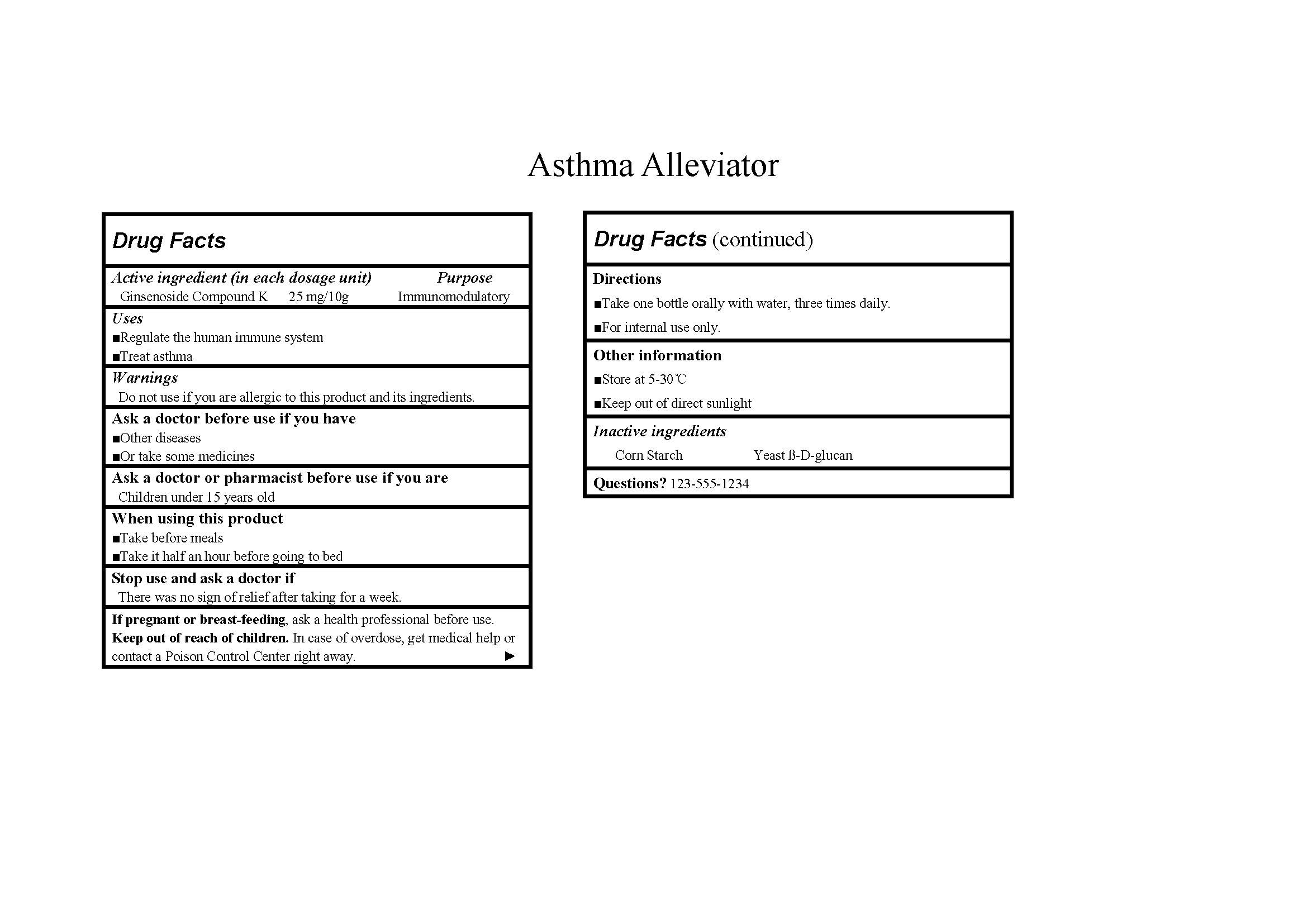 DRUG LABEL: Asthma Alleviator
NDC: 84428-101 | Form: GRANULE
Manufacturer: Hainan Zehuitang Biotechnology Co., LTD
Category: otc | Type: HUMAN OTC DRUG LABEL
Date: 20240624

ACTIVE INGREDIENTS: GINSENOSIDE COMPOUND K 25 mg/10 g
INACTIVE INGREDIENTS: YEAST .BETA.-D-GLUCAN; STARCH, CORN

84428-101-01

Active ingredient: Ginsenoside Compound K 25 mg/10g

Purpose: Immunomodulatory

INDICATIONS AND USAGE

Use to: Regulate the human immune system; Treat asthma

Do not use if you are allergic to this product and its ingredients.

Ask a doctor before use if you have：

Other diseases,

Or take some medicines

Ask a doctor or pharmacist before use if you are:

Children under 15 years old

When using this product:

Take before meals;

Take it half an hour before going to bed

Stop use and ask a doctor if There was no sign of relief after taking for a week.

PREGNANCY OR BREAST FEEDING

If pregnant or breast-feeding, ask a health professional before use.

Keep out of reach of children. In case of overdose, get medical help or contact a Poison Control Center right away.

Directions：

Take one bottle orally with water, three times daily, For internal use only.

Inactive ingredients: Corn Starch, Yeast ß-D-glucan

Questions? 123-555-1234

Other information: Store at 5-30℃, Keep out of direct sunlight

Label